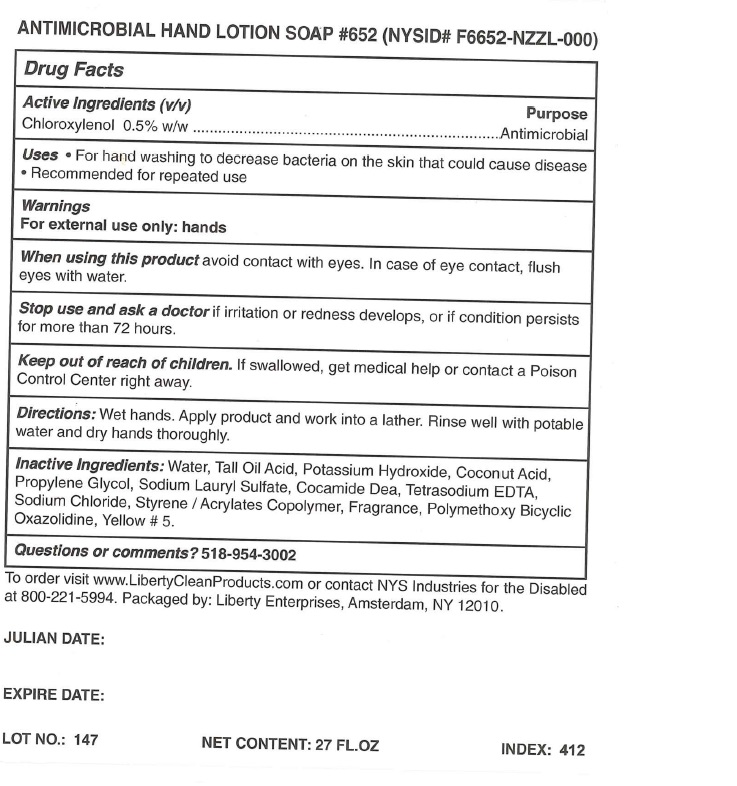 DRUG LABEL: Antimicrobial 652
NDC: 54679-0001 | Form: LOTION
Manufacturer: Montgomery County Chapter Nysarc, Inc dba Liberty Enterprises
Category: otc | Type: HUMAN OTC DRUG LABEL
Date: 20241014

ACTIVE INGREDIENTS: CHLOROXYLENOL 3.6 mg/800 mL
INACTIVE INGREDIENTS: WATER; TALL OIL ACID; POTASSIUM HYDROXIDE; COCONUT ACID; PROPYLENE GLYCOL; SODIUM LAURETH SULFATE; COCO DIETHANOLAMIDE; EDETATE SODIUM; SODIUM CHLORIDE; STYRENE/ACRYLAMIDE COPOLYMER (MW 500000); 5-HYDROXYMETHYL(METHYLENEOXY)-1-AZA-3,7-DIOXABICYCLO(3,3,0)OCTANE; FD&C YELLOW NO. 5

ACTIVE INGREDIENT:

CHLOROXYLENOL

Purpose

Antimicrobial

Uses

Antimicrobial hand sanitizer.

INACTIVE INGREDIENTS:

WATER, TALL OIL ACID, POTASSIUM HYDROXIDE, COCONUT ACID, PROPYLENE GLYCOL, SODIUM LAURYL SULFATE, COCAMIDE DEA, TETRASODIUM EDTA, SODIUM CHLORIDE, STYRENE/ACRYLATES COPOLYMER, FRAGRANCE, POLYMETHOXY BICYLIC OXAZOLIDINE, YELLOW 5.

DIRECTIONS:

Dispense sufficient amount onto hands, add water, lather, and rinse.

WARNING:

FOR EXTERNAL USE ONLY. Avoid contact witheyes. In case of eye contact, immediately flush with water. If eye or skin irritation persists, get medical advice/attention. If ingested, contact a physician or Poison Control Center immediately.

Keep out of reach of children.

INACTIVE INGREDIENT

Inactive ingredients - Water, Tall oil acid, Potasium hydroxide, Coconut acid, Propylene glycol,

Sodium lauryl sulfate, Cocamide DEA, Tetrasodium EDTA, Sodium chloride, Styrene/Acrylates Copolymer,

Fragrence, Polymethoxy biclic oxazolidine, Yellow 5.

ANTIMICROBIAL HAND LOTION SOAP product label

ANTIMICROBIAL HAND LOTION SOAP #652 (NYSID # F6652)

To order visit www.LibertyCleanProducts.com or contact NYS Industries for the Disabled at 800-221-5994. Packaged by: Liberty Enterprises, Amsterdam, NY 12010

res